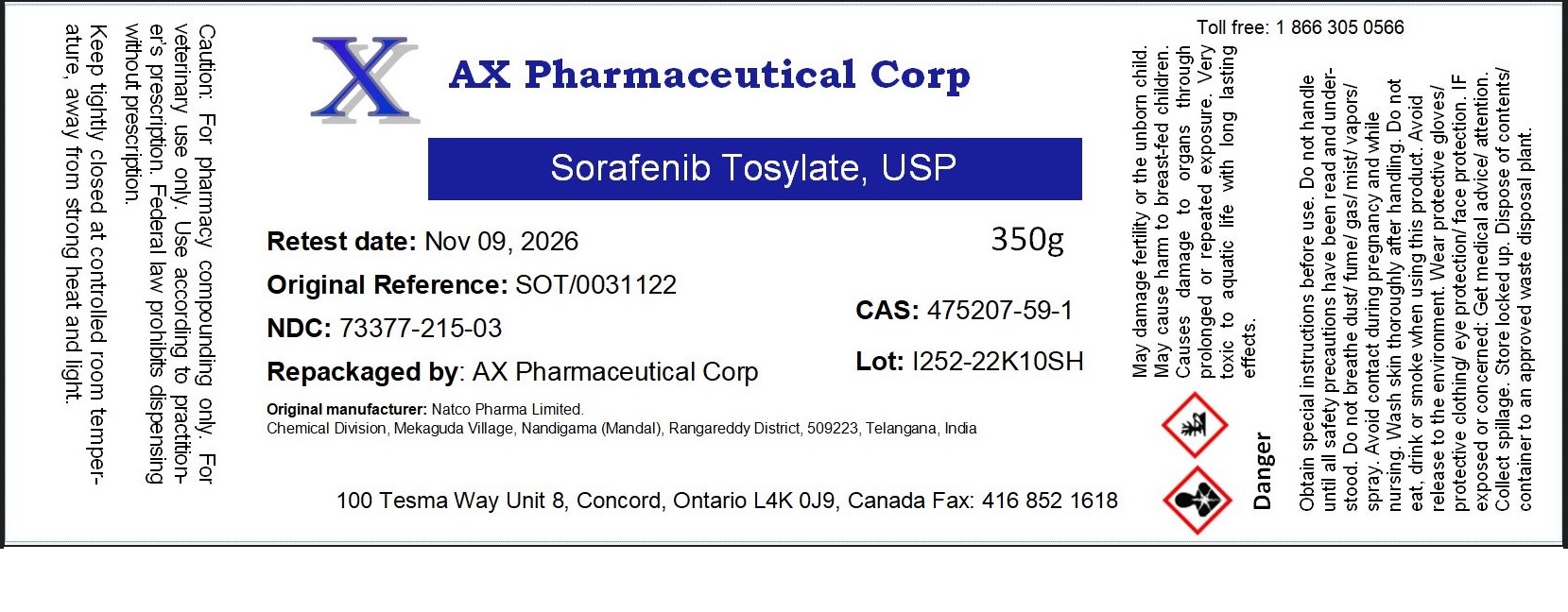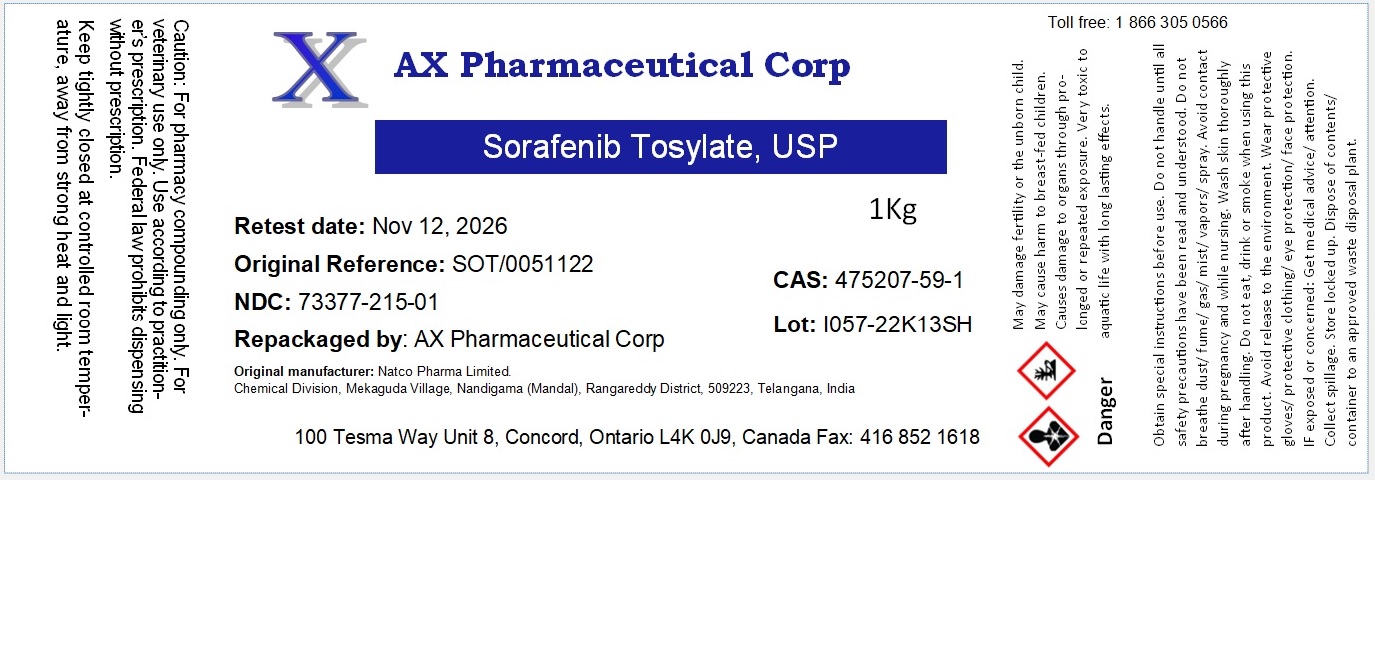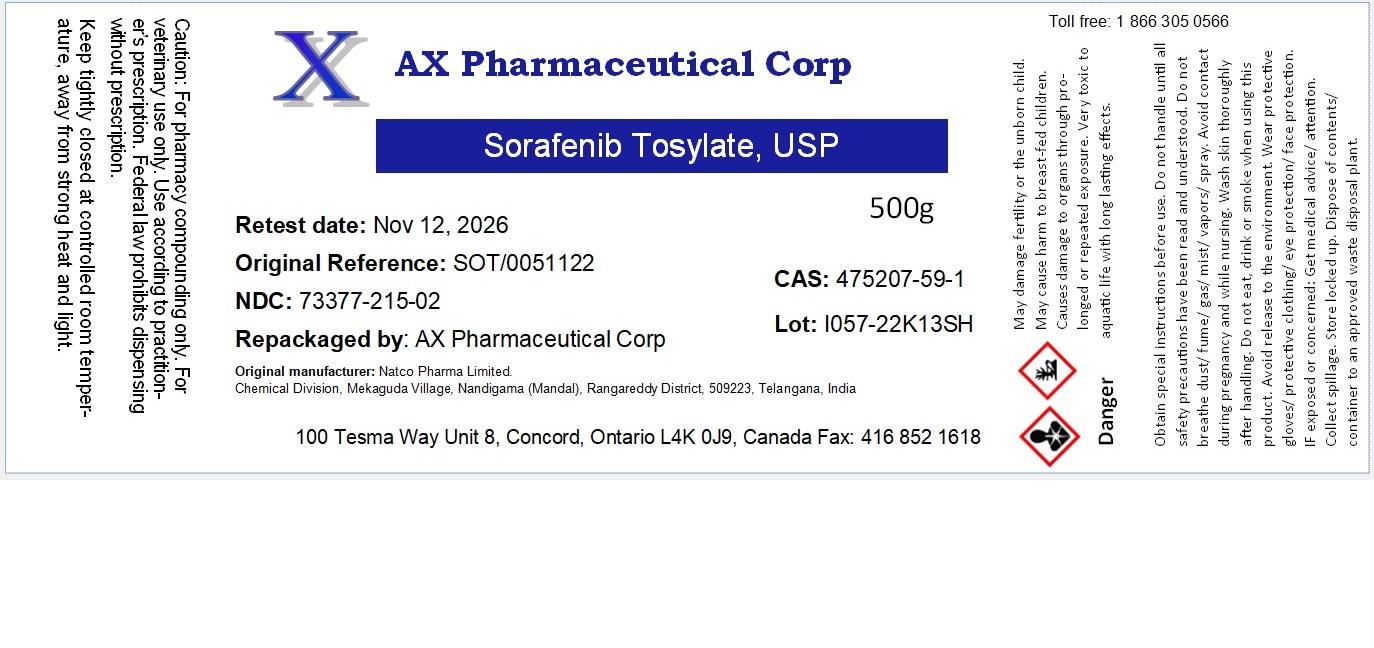 DRUG LABEL: sorafenib Tosylate
NDC: 73377-215 | Form: POWDER
Manufacturer: AX Pharmaceutical Corp
Category: other | Type: BULK INGREDIENT - ANIMAL DRUG
Date: 20230829

ACTIVE INGREDIENTS: SORAFENIB TOSYLATE 1 g/1 g

Sorafenib Tosylate